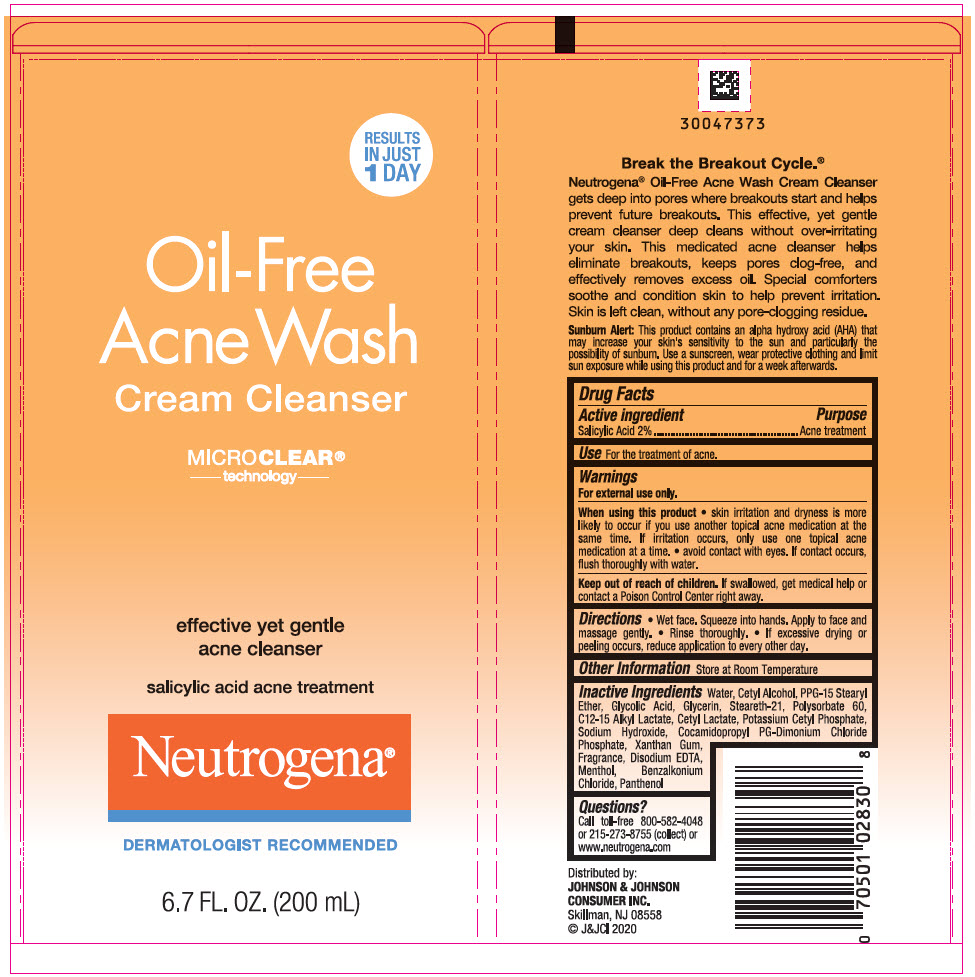 DRUG LABEL: Neutrogena Oil Free Acne Wash Cleanser
NDC: 69968-0155 | Form: CREAM
Manufacturer: Kenvue Brands LLC
Category: otc | Type: HUMAN OTC DRUG LABEL
Date: 20241111

ACTIVE INGREDIENTS: SALICYLIC ACID 20 mg/1 mL
INACTIVE INGREDIENTS: WATER; CETYL ALCOHOL; PPG-15 STEARYL ETHER; GLYCOLIC ACID; GLYCERIN; STEARETH-21; POLYSORBATE 60; C12-15 ALKYL LACTATE; CETYL LACTATE; POTASSIUM CETYL PHOSPHATE; SODIUM HYDROXIDE; COCAMIDOPROPYL PROPYLENE GLYCOL-DIMONIUM CHLORIDE PHOSPHATE; XANTHAN GUM; EDETATE DISODIUM; MENTHOL, UNSPECIFIED FORM; BENZALKONIUM CHLORIDE; PANTHENOL

Neutrogena® Oil-Free Acne Wash Cream Cleanser

Drug Facts

Active ingredient

Salicylic Acid 2%

Purpose

Acne treatment

Use

For the treatment of acne.

Warnings

For external use only.

When using this product

- skin irritation and dryness is more likely to occur if you use another topical acne medication at the same time. If irritation occurs, only use one topical acne medication at a time.
- avoid contact with eyes. If contact occurs, flush thoroughly with water.

Keep out of reach of children. If swallowed, get medical help or contact a Poison Control Center right away.

Directions

- Wet face. Squeeze into hands. Apply to face and massage gently.
- Rinse thoroughly.
- If excess drying or peeling occurs, reduce application to every other day.

Other information

Store at Room Temperature

Inactive ingredients

Water, Cetyl Alcohol, PPG-15 Stearyl Ether, Glycolic Acid, Glycerin, Steareth-21, Polysorbate 60, C12-15 Alkyl Lactate, Cetyl Lactate, Potassium Cetyl Phosphate, Sodium Hydroxide, Cocamidopropyl PG-Dimonium Chloride Phosphate, Xanthan Gum, Fragrance, Disodium EDTA, Menthol, Benzalkonium Chloride, Panthenol

Questions?

Call toll-free 800-582-4048 or 215-273-8755 (collect) or www.neutrogena.com

Distributed by:
JOHNSON & JOHNSON
CONSUMER INC.
Skillman, NJ 08558

PRINCIPAL DISPLAY PANEL - 200 mL Tube Label

RESULTS
IN JUST
1 DAY

Oil-Free
Acne Wash
Cream Cleanser

MICRO CLEAR®
technology

effective yet gentle
acne cleanser

salicylic acid acne treatment

Neutrogena®
DERMATOLOGIST RECOMMENDED

6.7 FL. OZ. (200mL)